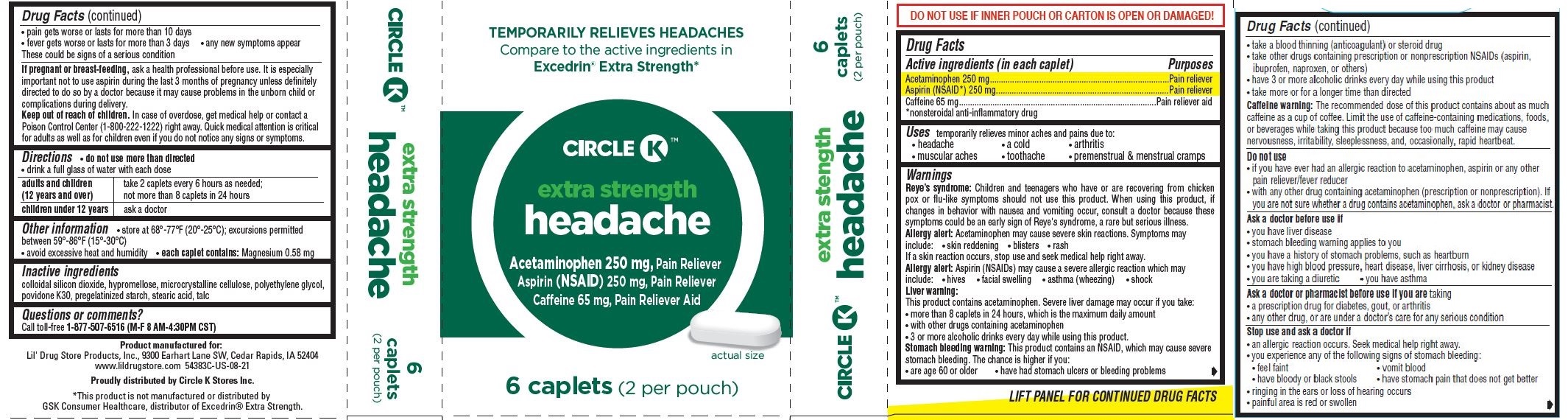 DRUG LABEL: Headache, Circle K
NDC: 66715-5438 | Form: TABLET
Manufacturer: Lil' Drug Store Products, Inc.
Category: otc | Type: HUMAN OTC DRUG LABEL
Date: 20241231

ACTIVE INGREDIENTS: ACETAMINOPHEN 250 mg/1 1; ASPIRIN 250 mg/1 1; CAFFEINE 65 mg/1 1
INACTIVE INGREDIENTS: CELLULOSE, MICROCRYSTALLINE; HYPROMELLOSE, UNSPECIFIED; POLYETHYLENE GLYCOL, UNSPECIFIED; POVIDONE K30; SILICON DIOXIDE; STARCH, CORN; STEARIC ACID; TALC

Headache, Circle K™

Active ingredients

Active ingredients (in each caplet)

Acetaminophen 250 mg

Aspirin (NSAID*) 250 mg

Caffeine 65 mg

*nonsteroidal anti-inflammatory drug

Purposes

Pain reliever

Pain reliever

Pain reliever aid

Uses

temporarily relieves minor aches and pains due to:

- headache
- a cold
- arthritis
- muscular aches
- toothache
- premenstrual & menstrual cramps

Warnings

Reye’s syndrome: Children and teenagers who have or are recovering from chicken pox or flu-like symptoms should not use this product. When using this product, if changes in behavior with nausea and vomiting occur, consult a doctor because these symptoms could be an early sign of Reye's syndrome, a rare but serious illness.

Allergy alert

Allergy alert: Acetaminophen may cause severe skin reactions. Symptoms may include:

- skin reddening
- blisters
- rash

If a skin reaction occurs, stop use and seek medical help right away.

Stomach bleeding warning: This product contains an NSAID, which may cause severe stomach bleeding. The chance is higher if you:

- are age 60 or olde
- have had stomach ulcers or bleeding problems
- pain gets worse or lasts for more than 10 days
- fever gets worse or lasts for more than 3 days
- any new symptoms appear

These could be signs of a serious condition

PREGNANCY OR BREAST FEEDING

If pregnant or breast-feeding, ask a health professional before use. It is especially important not to use aspirin during the last 3 months of pregnancy unless definitely directed to do so by a doctor because it may cause problems in the unborn child or complications during delivery.

Keep out of reach of children. In case of overdose, get medical help or contact a Poison Control Center (1-800-222-1222) right away. Quick medical attention is critical for adults as well as for children even if you do not notice any signs or symptoms.

Directions

- do not use more than directed
- drink a full glass of water with each dose

adults and children; (12 years and over) | take 2 capletsevery 6 hours as needed;; not more than 8 caplets in 24 hours
children under 12 years | ask a doctor

Other information

- store at 68°-77°F (20°-25°C); excursions permitted between 59°-86°F (15°-30°C)
- avoid excessive heat and humidity
- each caplet contains: Magnesium 0.58 mg

Inactive ingredients

Inactive ingredients colloidal silicon dioxide, hypromellose, microcrystalline cellulose, polyethylene glycol, povidone K30, pregelatinized starch, stearic acid, talc

Questions or comments?

Call toll-free 1-877-507-6516 (M-F 8 AM-4:30PM CST)

Product manufactured for:
Lil' Drug Store Products, Inc., 9300 Earhart Lane SW, Cedar Rapids, IA 52404
www.lildrugstore.com 54383C-US-08-21

Proudly distributed by Circle K Stores Inc.

*This product is not manufactured or distributed by GSK Consumer Healthcare, distributor of Excedrin® Extra Strength.

PDP/Package

TEMPORARILY RELIEVES HEADACHES
Compare to the active ingredients in
Excedrin® Extra Strength*

CIRCLE K™

extra strength

headache

Acetaminophen 250 mg, Pain Reliever
Aspirin (NSAID) 250 mg, Pain Reliever
Caffeine 65 mg, Pain Reliever Aid

[caplet image]

actual size

6 caplets (2 per pouch)